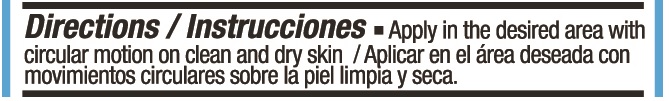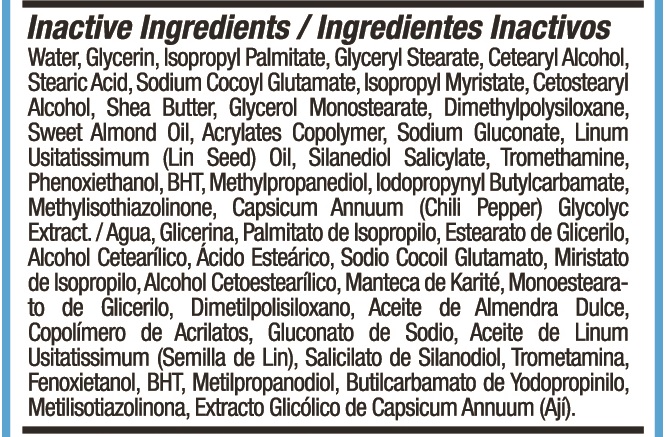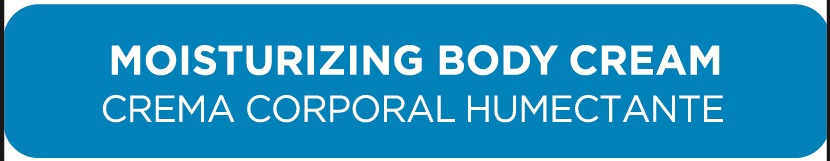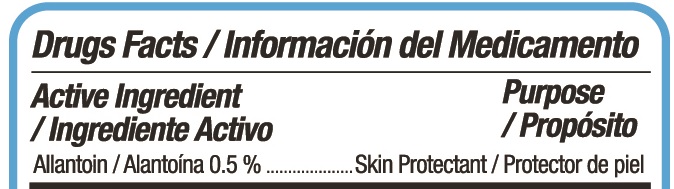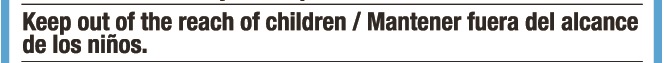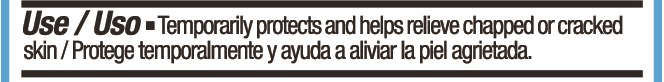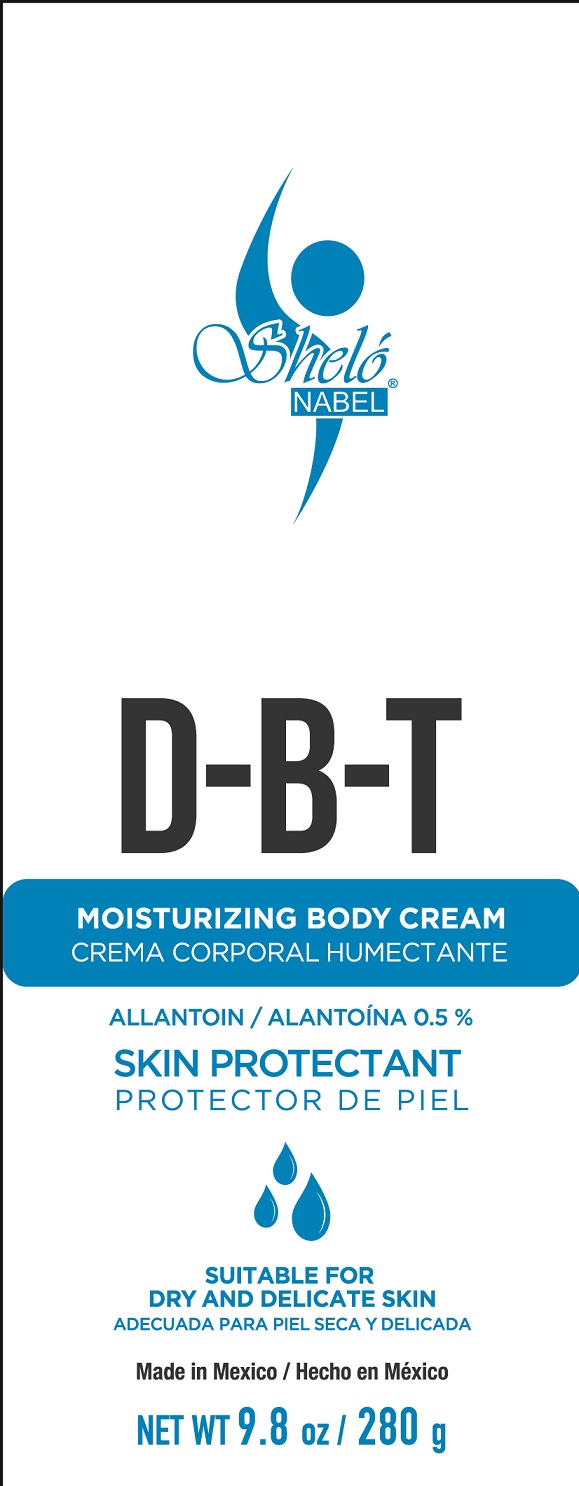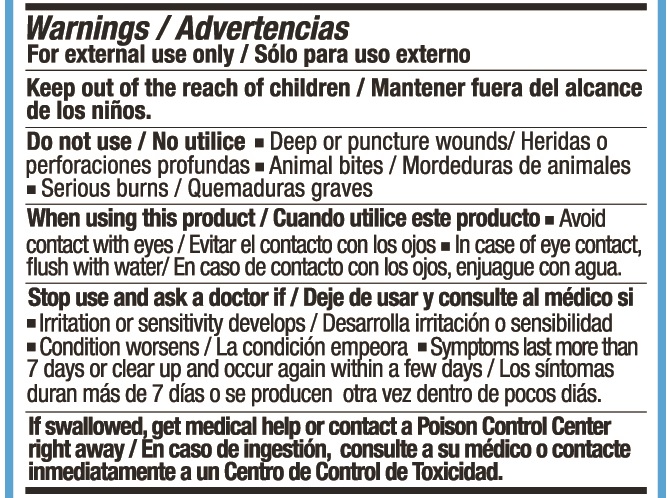 DRUG LABEL: Shelo NABEL D B T Cream
NDC: 71424-1145 | Form: CREAM
Manufacturer: Corporativo Serysi S de R L de C V
Category: otc | Type: HUMAN OTC DRUG LABEL
Date: 20191015

ACTIVE INGREDIENTS: ALLANTOIN 5 mg/1 g
INACTIVE INGREDIENTS: ISOPROPYL PALMITATE

Sheló NABEL D-B-T Cream